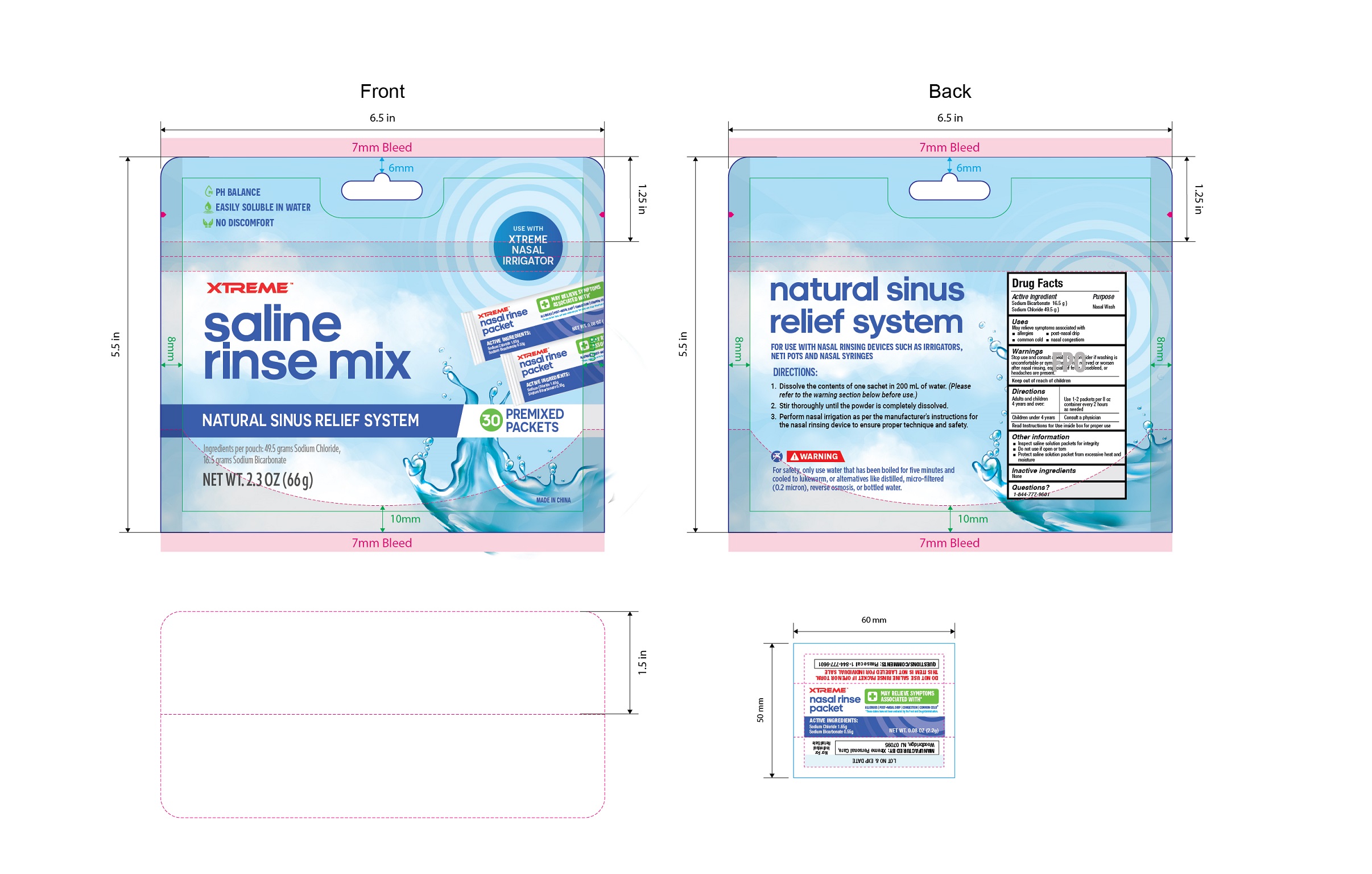 DRUG LABEL: NASAL RINES SALT
NDC: 85814-001 | Form: POWDER
Manufacturer: Onion Culture Industrial Co., Limited
Category: otc | Type: HUMAN OTC DRUG LABEL
Date: 20250617

ACTIVE INGREDIENTS: Sodium Chloride 49.5 g/100 g; Sodium Bicarbonate 16.5 g/100 g

Active ingredient

Sodium Bicarbonate 16.5 g Sodium Chloride 49.5 g

Purpose

Nasal Wash

Use

May relieve symptoms associated with

allergies post-nasal drip common cold nasal congestiom

Warnings

Stop use and consult consider if washing is uncomfortable after nasal rinsing.

Keep out of reach of children

Directions

Adults and children4 years and over：Use 1-2 packets per 8 ozcontainer every 2 hoursas needed

Children under 4 years：Consult a physician

Read Instructions for Use inside box for proper use

Other information

Inspect saline solution packets for integrity

Do not use if open or tom

Protect saline solurtion packet from excessive heat andmoisture

Inactive ingredients

none

Questions

1-844-777-9301